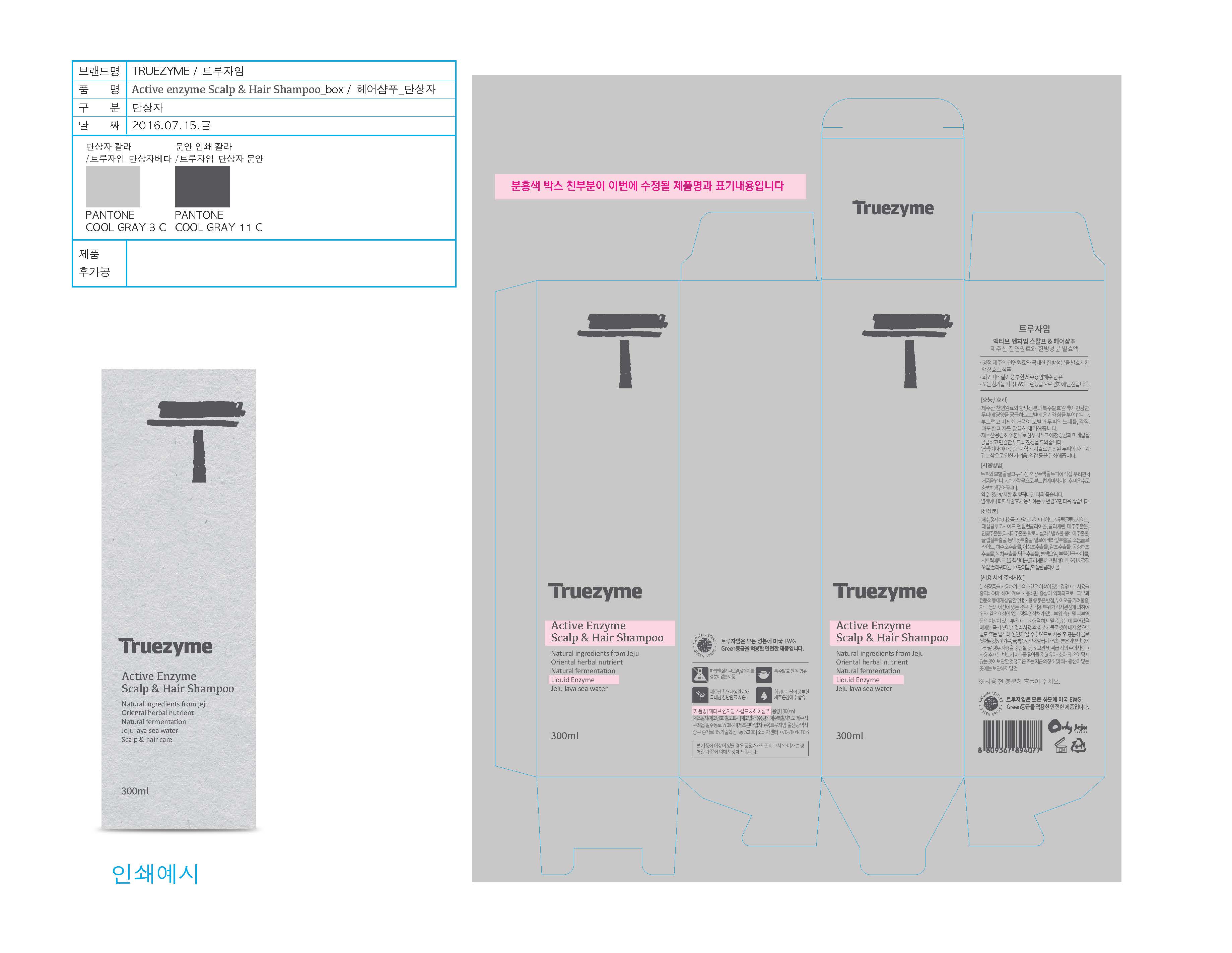 DRUG LABEL: Truezyme Active Enzyme Scalp and Hair
NDC: 71076-0004 | Form: SHAMPOO
Manufacturer: Truezyme Co., Ltd.
Category: otc | Type: HUMAN OTC DRUG LABEL
Date: 20161116

ACTIVE INGREDIENTS: GLYCERIN 2.5 g/100 mL
INACTIVE INGREDIENTS: PANTHENOL; ALOE VERA LEAF; LAURYL GLUCOSIDE

Drug Facts

Active ingredient

Glycerin

Purpose

Nourish the sensitive scalp and also make hair lustrous and strong

DOSAGE AND ADMINISTRATION

For external use only

INDICATIONS AND USAGE

- Wet the scalp and hair evenly and spray the product directly over the scalp and lather well. Massage the scalp with fingertips gently and wash with warm water enough,

- Leave for 2 or 3 minutes and then wash for better results.

- Shampoo twice after dyeing or chemical treatment for better results.

* Shake well before use.

Inactive ingredients:

Sea Water, Water, Lauryl Glucosie, Aloe Barbadensis Leaf Extract, Butylene Glycol, Panthenol, etc.

Keep out of reach of children.

WARNINGS

1. Stop using the product if there are any of the following abnormal symptoms appearing after use and consult with your dermatologist as continued use can worsen the symptoms.

1) If there are red spots, swelling, itchiness, or irritation

2) If the above symptoms appear around the skin to which the product has been applied after being exposed to direct sunlight.

2. Do not apply the product to any parts of the skin with wound, eczema, or dermatitis.

3. If it gets into eye, wash the eye with clean water immediately.

4. Those who are allergic to certain medicinal herb, such as pollen and tangerine, must stop using the product if they experience hypersensitivity.

5. Precautions on storage and handling

1) Make sure to close the cap after use.

2) Keep out of the reach of children.

3) Do not keep the product in a hot or cold place or a place getting direct sunlight.